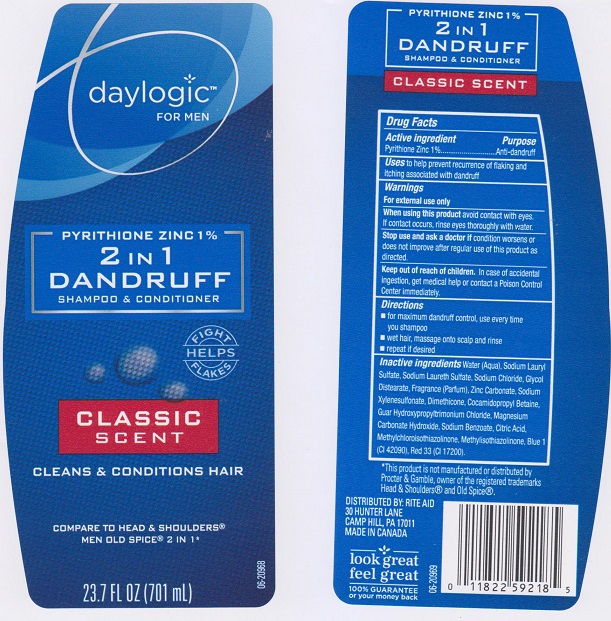 DRUG LABEL: Daylogic 2 in 1 Dandruff
NDC: 11822-4332 | Form: SHAMPOO
Manufacturer: Rite Aid Corporation
Category: otc | Type: HUMAN OTC DRUG LABEL
Date: 20160615

ACTIVE INGREDIENTS: PYRITHIONE ZINC 10 mg/1 mL
INACTIVE INGREDIENTS: WATER; SODIUM LAURYL SULFATE; SODIUM LAURETH SULFATE; SODIUM CHLORIDE; GLYCOL DISTEARATE; ZINC CARBONATE; SODIUM XYLENESULFONATE; DIMETHICONE; COCAMIDOPROPYL BETAINE; GUAR HYDROXYPROPYLTRIMONIUM CHLORIDE (1.7 SUBSTITUENTS PER SACCHARIDE); MAGNESIUM CARBONATE HYDROXIDE; SODIUM BENZOATE; CITRIC ACID ACETATE; METHYLCHLOROISOTHIAZOLINONE; METHYLISOTHIAZOLINONE; FD&C BLUE NO. 1; D&C RED NO. 33

DRUG FACTS

Active ingredient

Pyrithione Zinc 1%

Purpose

Anti-dandruff

Uses

to help prevent recurrence of flaking and itching associated with dandruff.

Warnings

For external use only.

When using this product

avoid contact with eyes. If contact occurs, rinse eyes thoroughly with water.

Stop use and ask a doctor if

condition worsens or does not improve after regular use of this product as directed.

Keep out of reach out of children.

In case of accidental ingestion, get medical help or contact a Poison Control Center immediately.

Directions

- for maximum dandruff control, use every time you shampoo.
- wet hair, massage onto scalp and rinse.
- repeat if desired.

Inactive ingredients

Water (Aqua), Sodium Lauryl Sulfate, Sodium Laureth Sulfate, Sodium Chloride, Glycol Distearate, Fragrance (Parfum), Zinc Carbonate, Sodium Xylenesulfonate, Dimethicone, Cocamidopropyl Betaine, Guar Hydroxypropyltrimonium Chloride, Magnesium Carbonate Hydroxide, Sodium Benzoate, Citric Acid, Methylchloroisothiazolinone, Methylisothiazolinone, Blue 1 (CI 42090), Red 33 (CI 17200).